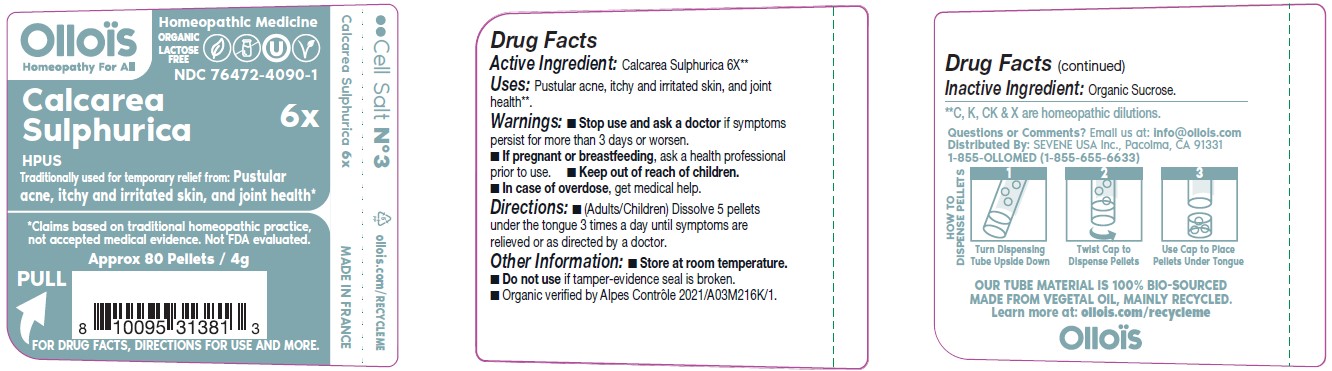 DRUG LABEL: CALCAREA SULPHURICA

NDC: 76472-4090 | Form: PELLET
Manufacturer: SEVENE USA
Category: homeopathic | Type: HUMAN OTC DRUG LABEL
Date: 20250211

ACTIVE INGREDIENTS: CALCIUM SULFATE ANHYDROUS 6 [hp_X]/1 1
INACTIVE INGREDIENTS: SUCROSE

SEVENE USA (as PLD) - CALCAREA SULPHURICA 6X (76472-4090)

ACTIVE INGREDIENT:

CALCAREA SULPHURICA 6X**

TRADITIONALLY USED FOR TEMPORARY RELIEF FROM:

Pustular acne, itchy and irritated skin, and joint health*

*Claims based on traditional homeopathic practice, not accepted medical evidence. Not FDA evaluated.

DIRECTIONS:

- (Adults/Children) Dissolve 5 pellets under the tongue three times a day until symptoms are relieved or as directed by a doctor.

USES:

Pustular acne, itchy and irritated skin, and joint health**.

**C, K, CK & X are homeopathic dilutions.

WARNINGS

- Stop use and ask a doctor if symptoms persist for more than 3 days or worsen.

PREGNANCY OR BREAST FEEDING

- If pregnant or breast-feeding, ask a health professional before use.

- Keep out of reach of children.
- In case of overdose, get medical help.

OTHER INFORMATION:

- Store at room temperature.
- Do not use if tamper-evidence seal is broken.
- Organic verified by Alpes Control 2021/A03M216K/1.

INACTIVE INGREDIENT:

ORGANIC SUCROSE

QUESTIONS OR COMMENTS?

Email us at: info@ollois.com